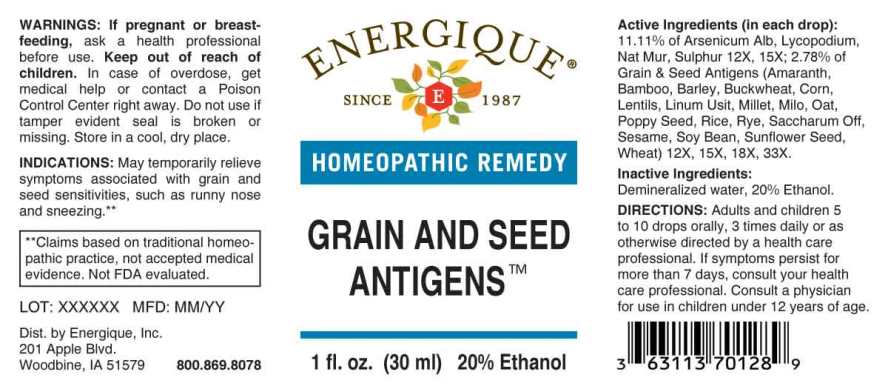 DRUG LABEL: Grain and Seed Antigens
NDC: 44911-0637 | Form: LIQUID
Manufacturer: Energique, Inc.
Category: homeopathic | Type: HUMAN OTC DRUG LABEL
Date: 20241025

ACTIVE INGREDIENTS: BAMBUSA VULGARIS TOP 12 [hp_X]/1 mL; BARLEY 12 [hp_X]/1 mL; CORN 12 [hp_X]/1 mL; COTTON SEED 12 [hp_X]/1 mL; FLAX SEED 12 [hp_X]/1 mL; BUCKWHEAT 12 [hp_X]/1 mL; MILLET 12 [hp_X]/1 mL; SORGHUM BICOLOR WHOLE 12 [hp_X]/1 mL; OAT 12 [hp_X]/1 mL; WHITE RICE 12 [hp_X]/1 mL; RYE 12 [hp_X]/1 mL; LENTIL 12 [hp_X]/1 mL; SESAMUM INDICUM WHOLE 12 [hp_X]/1 mL; AMARANTH 12 [hp_X]/1 mL; SOYBEAN 12 [hp_X]/1 mL; SUCROSE 12 [hp_X]/1 mL; SUNFLOWER SEED 12 [hp_X]/1 mL; WHEAT 12 [hp_X]/1 mL
INACTIVE INGREDIENTS: WATER; ALCOHOL

DRUG FACTS:

ACTIVE INGREDIENTS:

(in each drop): 11.11% of Arsenicum Album 12X, 15X, Lycopodium Clavatum 12X, 15X, Natrum Muriaticum 12X, 15X, Sulphur 12X, 15X; 2.78% of Bamboo 12X, 15X, 18X, 33X, Barley 12X, 15X, 18X, 33X, Corn 12X, 15X, 18X, 33X, Cotton Seed 12X, 15X, 18X, 33X, Flax Seed (Linum Usitatissimum) 12X, 15X, 18X, 33X, Millet 12X, 15X, 18X, 33X, Milo 12X, 15X, 18X, 33X, Oat 12X, 15X, 18X, 33X, Poppy Seed 12X, 15X, 18X, 33X, Rice 12X, 15X, 18X, 33X, Rye 12X, 15X, 18X, 33X, Safflower 12X, 15X, 18X, 33X, Sesame 12X, 15X, 18X, 33X, Sorghum 12X, 15X, 18X, 33X, Soy Bean 12X, 15X, 18X, 33X, Sugarcane 12X, 15X, 18X, 33X, Sunflower (Helianthus Annuus) 12X, 15X, 18X, 33X, Wheat 12X, 15X, 18X, 33X.

INDICATIONS:

May temporarily relieve symptoms associated with grains and seed allergies such as runny nose and sneezing.**

**Claims based on traditional homeopathic practice, not accepted medical evidence. Not FDA evaluated.

WARNINGS:

If pregnant or breastfeeding, ask a health professional before use.

Keep out of reach of children. In case of overdose, get medical help or contact a Poison Control Center right away.

Do not use if tamper evident seal is broken or missing.

Store in a cool, dry place.

Keep out of reach of children. In case of overdose, get medical help or contact a Poison Control Center right away.

DIRECTIONS:

Adults and children 5 to 10 drops orally, 3 times daily or as otherwise directed by a health care professional. If symptoms persist for more than 7 days, consult your health care professional. Consult a physician for use in children under 12 years of age.

INDICATIONS:

May temporarily relieve symptoms associated with grains and seed allergies such as runny nose and sneezing.**

**Claims based on traditional homeopathic practice, not accepted medical evidence. Not FDA evaluated.

INACTIVE INGREDIENTS:

Demineralized water, 20% Ethanol

QUESTIONS:

Dist. by Energique, Inc.
201 Apple Blvd.
Woodbine, IA 51579 800.869.8078

PACKAGE LABEL DISPLAY:

ENERGIQUE

SINCE 1987

HOMEOPATHIC REMEDY

GRAIN AND SEED

ANTIGENS

1 fl. oz. (30 ml)